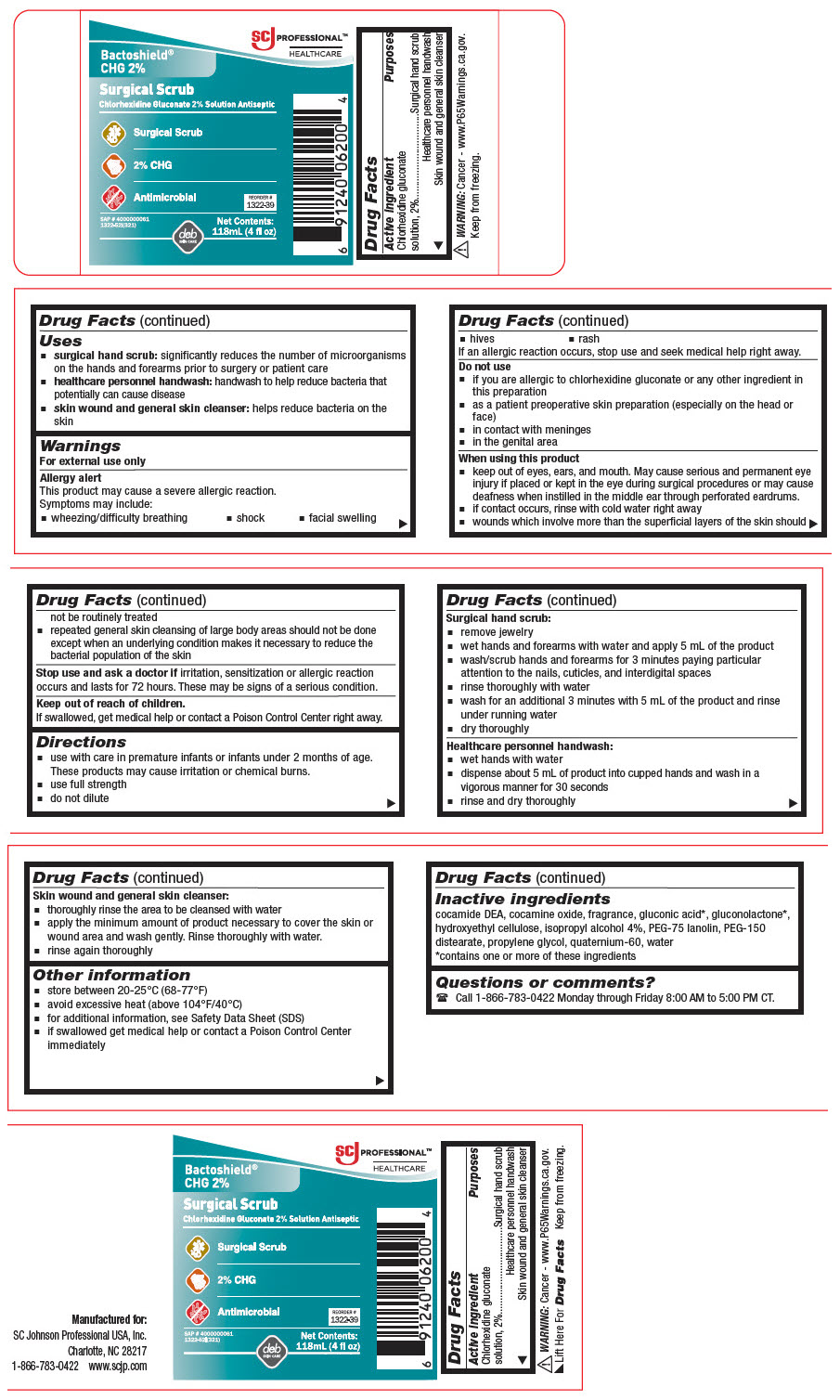 DRUG LABEL: Bactoshield CHG
NDC: 11084-126 | Form: LIQUID
Manufacturer: SC Johnson Professional USA, Inc.
Category: otc | Type: HUMAN OTC DRUG LABEL
Date: 20250709

ACTIVE INGREDIENTS: CHLORHEXIDINE GLUCONATE 20 mg/1 mL
INACTIVE INGREDIENTS: WATER; COCO DIETHANOLAMIDE; COCAMINE OXIDE; GLUCONIC ACID; GLUCONOLACTONE; HYDROXYETHYL CELLULOSE (5000 MPA.S AT 1%); ISOPROPYL ALCOHOL; PEG-75 LANOLIN; PEG-150 DISTEARATE; PROPYLENE GLYCOL; Quaternium-33

Bactoshield® CHG 2%

Drug Facts

Active ingredient

Chlorhexidine gluconate solution, 2%

Purposes

Surgical hand scrub

Healthcare personnel handwash

Skin wound and general skin cleanser

Uses

- surgical hand scrub: significantly reduces the number of microorganisms on the hands and forearms prior to surgery or patient care
- healthcare personnel handwash: handwash to help reduce bacteria that potentially can cause disease
- skin wound and general skin cleanser: helps reduce bacteria on the skin

Warnings

For external use only

Allergy alert

This product may cause a severe allergic reaction. Symptoms may include:

- wheezing/difficulty breathing
- shock
- facial swelling
- hives
- rash

If an allergic reaction occurs, stop use and seek medical help right away.

Do not use

- if you are allergic to chlorhexidine gluconate or any other ingredient in this preparation
- as a patient preoperative skin preparation (especially on the head or face)
- in contact with meninges
- in the genital area

When using this product

- keep out of eyes, ears, and mouth. May cause serious and permanent eye injury if placed or kept in the eye during surgical procedures or may cause deafness when instilled in the middle ear through perforated eardrums.
- if contact occurs, rinse with cold water right away
- wounds which involve more than the superficial layers of the skin should not be routinely treated
- repeated general skin cleansing of large body areas should not be done except when an underlying condition makes it necessary to reduce the bacterial population of the skin

Stop use and ask a doctor if irritation, sensitization or allergic reaction occurs and lasts for 72 hours. These may be signs of a serious condition.

Keep out of reach of children.

If swallowed, get medical help or contact a Poison Control Center right away.

Directions

- use with care in premature infants or infants under 2 months of age. These products may cause irritation or chemical burns.
- use full strength
- do not dilute

Surgical hand scrub

- remove jewelry
- wet hands and forearms with water and apply 5 mL of the product
- wash/scrub hands and forearms for 3 minutes paying particular attention to the nails, cuticles, and interdigital spaces
- rinse thoroughly with water
- wash for an additional 3 minutes with 5 mL of the product and rinse under running water
- dry thoroughly

Healthcare personnel handwash

- wet hands with water
- dispense about 5 mL of product into cupped hands and wash in a vigorous manner for 30 seconds
- rinse and dry thoroughly

Skin wound and general skin cleanser

- thoroughly rinse the area to be cleansed with water
- apply the minimum amount of product necessary to cover the skin or wound area and wash gently. Rinse thoroughly with water.
- rinse again thoroughly

Other information

- store between 20-25°C (68-77°F)
- avoid excessive heat (above 104°F/40°C)
- for additional information, see Safety Data Sheet (SDS)
- if swallowed get medical help or contact a Poison Control Center immediately

Inactive ingredients

cocamide DEA, cocamine oxide, fragrance, gluconic acid [contains one or more of these ingredients] , gluconolactone, hydroxyethyl cellulose, isopropyl alcohol 4%, PEG-75 lanolin, PEG-150 distearate, propylene glycol, quaternium-60, water

Questions or comments?

Call 1-866-783-0422 Monday through Friday 8:00 AM to 5:00 PM CT.

PRINCIPAL DISPLAY PANEL - 118 mL Bottle Label

SCJ PROFESSIONAL™
HEALTHCARE

Bactoshield®
CHG 2%

Surgical Scrub
Chlorhexidine Gluconate 2% Solution Antiseptic

Surgical Scrub

2% CHG

Antimicrobial

REORDER #
1322-39

SAP # 4000000061
1322-52l(321)

Net Contents:
118mL (4 fl oz)

deb
SKIN CARE